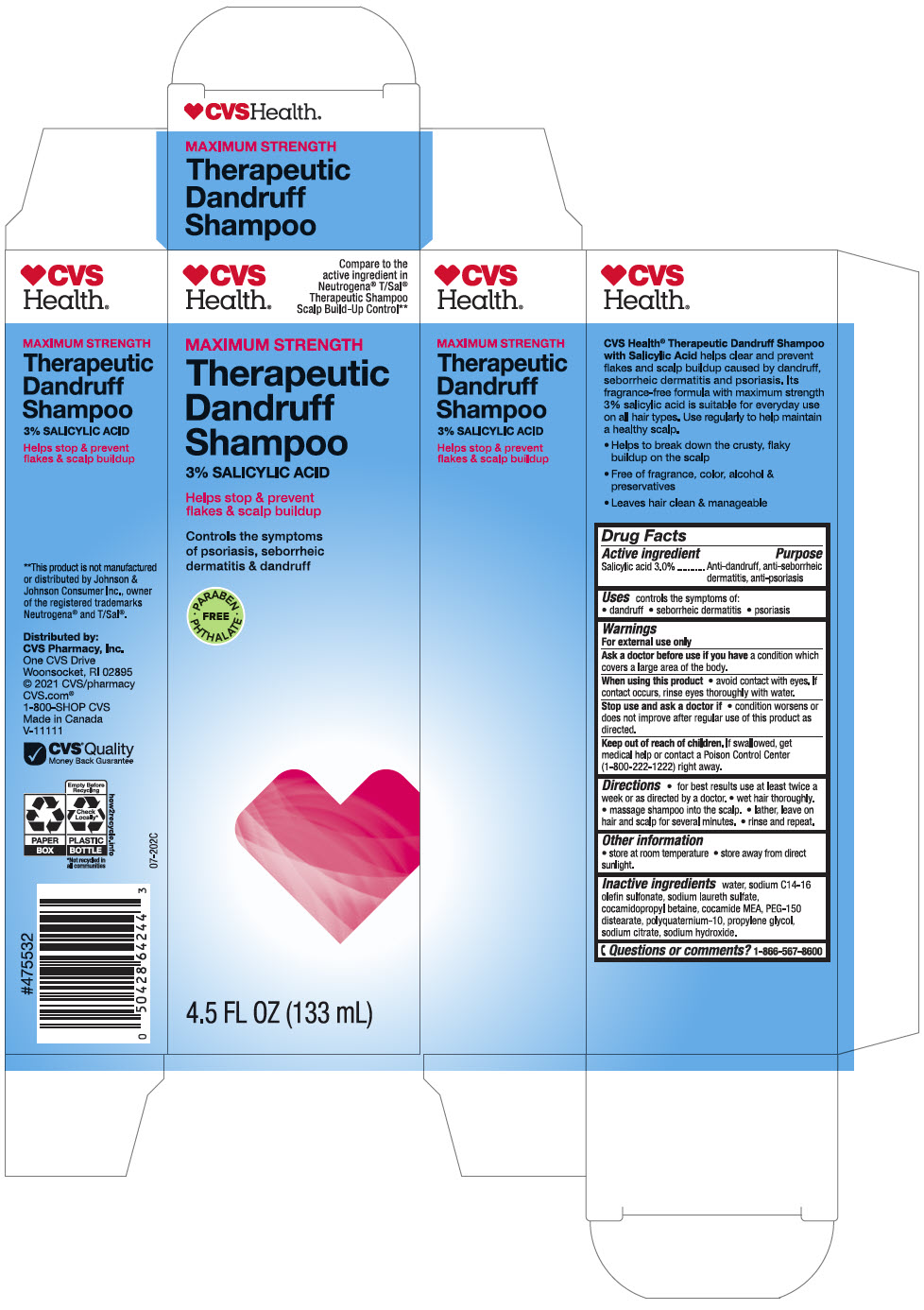 DRUG LABEL: CVS Health MAXIMUM STRENGTH Therapeutic Dandruff
NDC: 51316-443 | Form: SHAMPOO
Manufacturer: CVS Health
Category: otc | Type: HUMAN OTC DRUG LABEL
Date: 20240924

ACTIVE INGREDIENTS: SALICYLIC ACID 30 mg/1 mL
INACTIVE INGREDIENTS: Water; Sodium C14-16 Olefin Sulfonate; SODIUM LAURETH-3 SULFATE; Cocamidopropyl Betaine; COCO MONOETHANOLAMIDE; PEG-150 Distearate; POLYQUATERNIUM-10 (30000 MPA.S AT 2%); Propylene Glycol; SODIUM CITRATE, UNSPECIFIED FORM; Sodium Hydroxide

CVS Health® MAXIMUM STRENGTH Therapeutic Dandruff Shampoo
Anti-dandruff, anti-seborrheic dermatitis, anti-psoriasis

Drug Facts

Active ingredient

Salicylic acid 3.0%

Purpose

Anti-dandruff, anti-seborrheic dermatitis, anti-psoriasis

Uses

controls the symptom of:

- dandruff
- seborrheic dermatitis
- psoriasis

Warnings

For external use only.

Ask a doctor before use if you have a condition that covers a large area of the body.

When using this product

- avoid contact with the eyes. If contact occurs, rinse eyes thoroughly with water.

Stop use and ask a doctor if

- condition worsens or does not improve after regular use of this product as directed.

Keep out of reach of children. If swallowed, get medical help or contact a Poison Control Center (1-800-222-1222) right away.

Directions

- for best results use at least twice a week or as directed by a doctor.
- wet hair thoroughly.
- massage shampoo into the scalp.
- lather, leave on hair and scalp for several minutes.
- rinse and repeat.

Other information

- store at room temperature
- store away from direct sunlight

Inactive ingredients

water, sodium C14-16 olefin sulfonate, sodium laureth sulfate, cocamidopropyl betaine, cocamide MEA, PEG-150 distearate, polyquaternium-10, propylene glycol, sodium citrate, sodium hydroxide

Questions or comments?

1-866-567-8600

Distributed by:
CVS Pharmacy, Inc.
One CVS Drive
Woonsocket, RI 02895

PRINCIPAL DISPLAY PANEL - 133 mL Bottle Carton

CVS
Health®

Compare to the
active ingredient in
Neutrogena® T/Sal®
Therapeutic Shampoo
Scalp Build-Up Control**

MAXIMUM STRENGTH

Therapeutic
Dandruff
Shampoo
3% SALICYLIC ACID

Helps stop & prevent
flakes & scalp buildup

Controls the symptoms
of psoriasis, seborrheic
dermatitis & dandruff

• PARABEN
PHTHALATE •
FREE

4.5 FL OZ (133 mL)